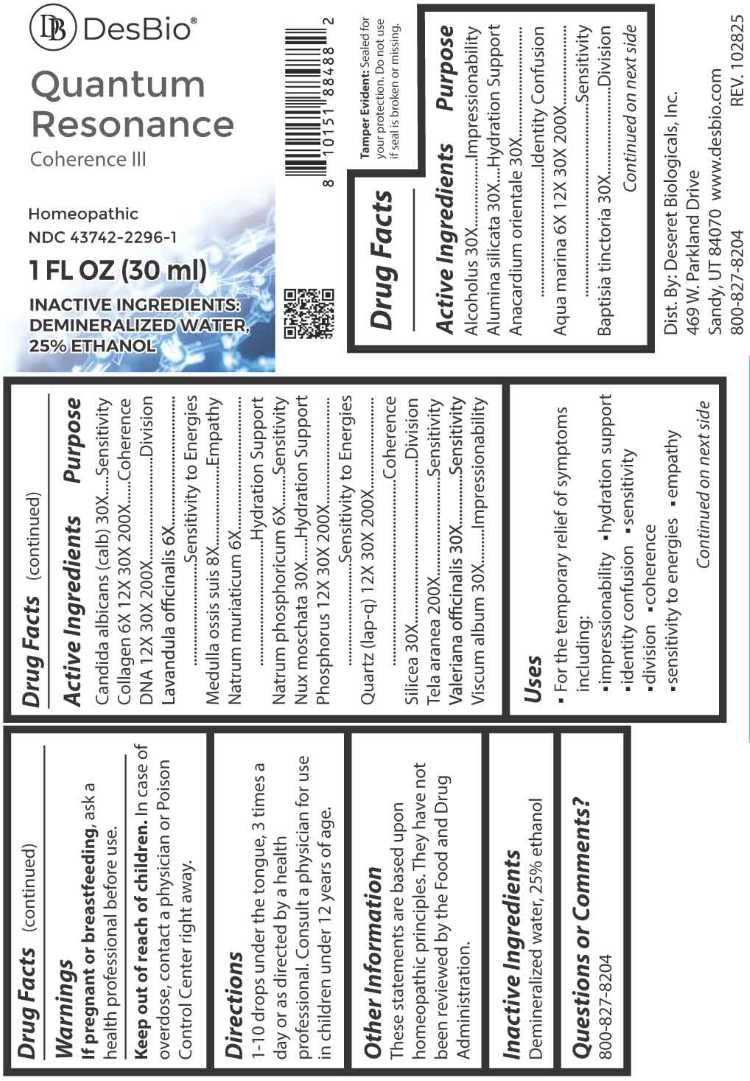 DRUG LABEL: Quantum Resonance
NDC: 43742-2296 | Form: LIQUID
Manufacturer: Deseret Biologicals, Inc.
Category: homeopathic | Type: HUMAN OTC DRUG LABEL
Date: 20260225

ACTIVE INGREDIENTS: ALCOHOL 30 [hp_X]/1 mL; KAOLIN 30 [hp_X]/1 mL; SEMECARPUS ANACARDIUM JUICE 30 [hp_X]/1 mL; SODIUM CHLORIDE 6 [hp_X]/1 mL; BAPTISIA TINCTORIA WHOLE 30 [hp_X]/1 mL; CANDIDA ALBICANS 30 [hp_X]/1 mL; BOVINE TYPE I COLLAGEN 6 [hp_X]/1 mL; HERRING SPERM DNA 12 [hp_X]/1 mL; LAVANDULA ANGUSTIFOLIA SUBSP. ANGUSTIFOLIA FLOWER 6 [hp_X]/1 mL; SUS SCROFA BONE MARROW 8 [hp_X]/1 mL; SODIUM PHOSPHATE, DIBASIC, HEPTAHYDRATE 6 [hp_X]/1 mL; NUTMEG 30 [hp_X]/1 mL; PHOSPHORUS 12 [hp_X]/1 mL; SILICON DIOXIDE 12 [hp_X]/1 mL; BOMBYX MORI FIBER 200 [hp_X]/1 mL; VALERIAN 30 [hp_X]/1 mL; VISCUM ALBUM FRUITING TOP 30 [hp_X]/1 mL
INACTIVE INGREDIENTS: WATER

DRUG FACTS:

ACTIVE INGREDIENTS:

Alcoholus 30X , Alumina Silicata 30X, Anacardium Orientale 30X, Aqua Marina 6X, 12X, 30X, 200X, Baptisia Tinctoria 30X, Candida Albicans 30X, Collagen 6X, 12X, 30X, 200X, DNA 12X, 30X, 200X, Lavandula Officinalis 6X, Medulla Ossis Suis 8X, Natrum Muriaticum 6X, Natrum Phosphoricum 6X, Nux Moschata 30X, Phosphorus 12X, 30X, 200X, Quartz 12X, 30X, 200X, Silicea 30X, Tela Aranea 200X, Valeriana Officinalis 30X, Viscum Album 30X.

PURPOSE:

Alcoholus - Impressionability, Alumina Silicata – Hydration Support, Anacardium Orientale – Identity Confusion, Aqua Marina - Sensitivity, Baptisia Tinctoria - Division, Candida Albicans - Sensitivity, Collagen - Coherence, DNA - Division, Lavandula Officinalis – Sensitivity to Energies, Medulla Ossis Suis - Empathy, Natrum Muriaticum – Hydration Support, Natrum Phosphoricum - Sensitivity, Nux Moschata – Hydration Support, Phosphorus – Sensitivity to Energies, Quartz - Coherence, Silicea - Division, Tela Aranea - Sensitivity, Valeriana Officinalis - Sensitivity, Viscum Album - Impressionability

USES:

• For the temporary relief of symptoms including:

• impressionability • hydration support • identity confusion • sensitivity

• division • coherence • sensitivity to energies • empathy

These statements are based upon homeopathic principles. They have not been reviewed by the Food and Drug Administration.

WARNINGS:

If pregnant or breastfeeding, ask a health professional before use.

Keep out of reach of children. In case of overdose, contact a physician or Poison Control Center right away.

Tamper Evident: Sealed for your protection. Do not use if seal is broken or missing.

KEEP OUT OF REACH OF CHILDREN:

In case of overdose, contact a physician or Poison Control Center right away.

DIRECTIONS:

1-10 drops under the tongue, 3 times a day or as directed by a health professional. Consult a physician for use in children under 12 years of age.

INACTIVE INGREDIENTS:

Demineralized water, 25% ethanol

QUESTIONS:

Dist. By: Deseret Biologicals, Inc.

469 W. Parkland Drive

Sandy, UT 84070

www.desbio.com

800-827-8204

PACKAGE LABEL DISPLAY:

DesBio

Quantum Resonance

Coherence III

Homeopathic

NDC 43742-2296-1

1 FL OZ (30ml)